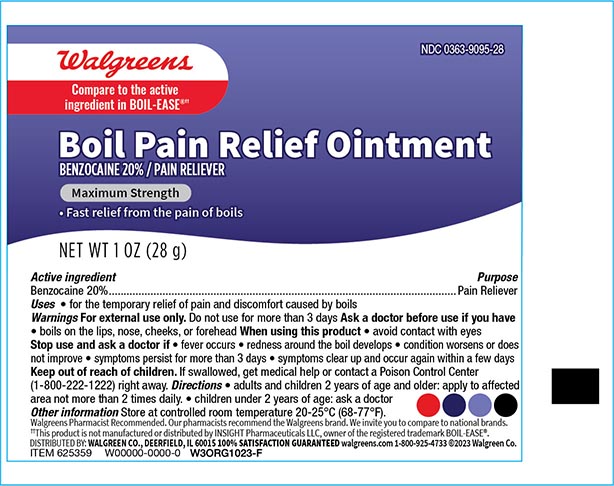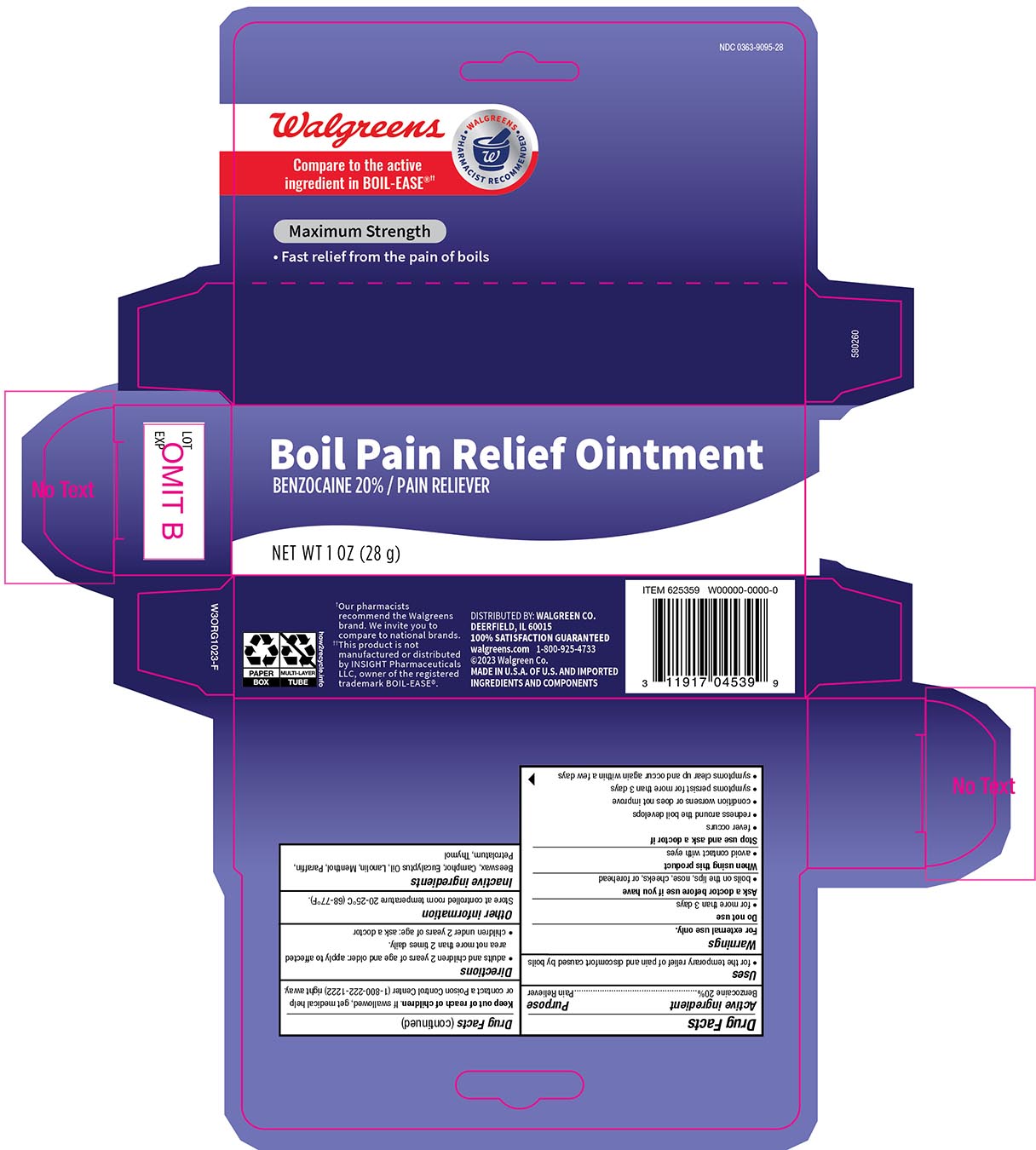 DRUG LABEL: Walgreens Boil Pain Relief
NDC: 0363-9095 | Form: OINTMENT
Manufacturer: Walgreens Company
Category: otc | Type: HUMAN OTC DRUG LABEL
Date: 20240212

ACTIVE INGREDIENTS: BENZOCAINE 200 mg/1 g
INACTIVE INGREDIENTS: SYNTHETIC BEESWAX; CAMPHOR (SYNTHETIC); EUCALYPTUS OIL; LANOLIN; MENTHOL; PARAFFIN; PETROLATUM; THYMOL

Walgreens Boil Pain Relief Ointment

Active Ingredient

Benzocaine 20%

Purpose

Pain Reliever

Uses

- for the temporary relief of pain and discomfort casued by boils

Do not use

- for more than 3 days

Ask a doctor before use if you have

- boils on the lips,nose ,cheeks or foreehead.

When using this product

- avoid contact with eyes

Stop use and ask a doctor if

- fevers occur
- redness around the bolis develops
- condition worsens or does not improve
- symptoms persist for mroe thna 3 days
- symptoms clear up and occur again within a few days.

KEEP OUT OF REACH OF CHILDREN

Keep out of the reach of childern. If swallowed, get medical help

or contact poison Control Center (1-800-222-1222) right away.

Directions

- Adults and children 2 years and older; Apply to the affected areas not more than 2 times daily
- Children under 2 years;ask a doctor

Other Information

Store as controlled room temperature 20-25 C (68-77F)

Inactive ingredients

Beeswax, Camphor, Eucalyptus Oil, Lanolin, Menthol, Paraffin, Petrolatum, Thymol

Principal display panel 1 oz

Walgreens NDC 0363-9095-28

Boil Pain Relief Ointment

Benzocaine 20%/ Pain reliever

NET WT 1 OZ (28g)